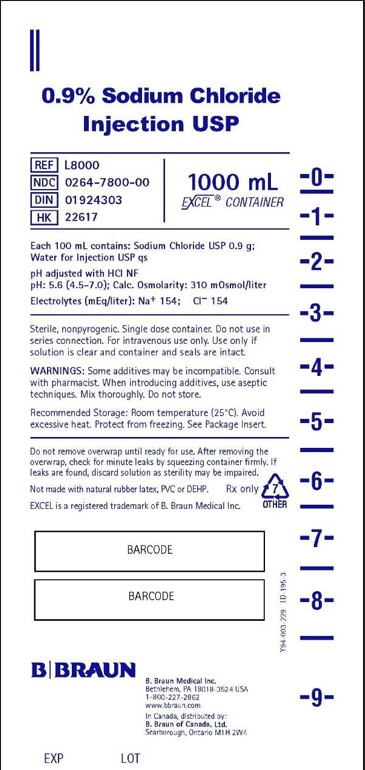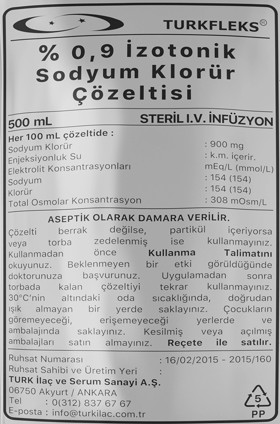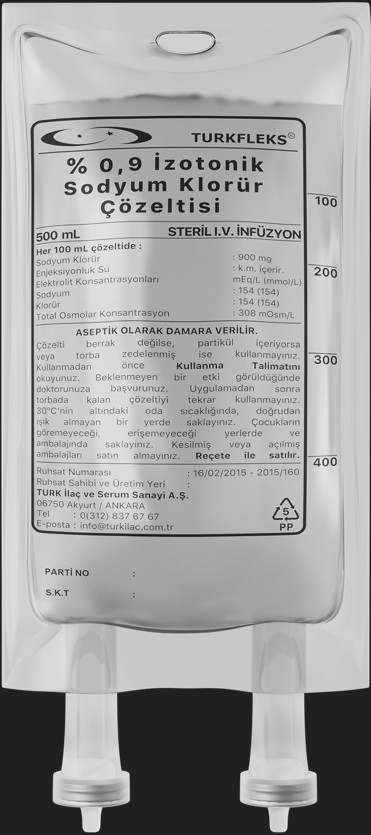 DRUG LABEL: TURKFLEKS 0.9%  ISOTONIC SODIUM CHLORIDE Solution
NDC: 85160-400 | Form: INJECTION, SOLUTION
Manufacturer: TURK ILAC VE SERUM SANAYI
Category: prescription | Type: HUMAN PRESCRIPTION DRUG LABEL
Date: 20250402

ACTIVE INGREDIENTS: CHLORIDE ION 0.9 g/100 mL

DESCRIPTION

NAME OF THE MEDICINAL PRODUCT
TURKFLEKS 0.9% ISOTONIC SODIUM CHLORIDE Solution

QUALITATIVE AND QUANTITATIVE COMPOSITION
Active substance:
Each 100 ml of solution contains 0.9 g sodium chloride.
Excipients: Water
Osmolarity of solution is 308 mOsmol/l.
Ionic concentrations of solution:
- sodium: 154 mEq/l
- chloride: 154 mEq/l

PHARMACEUTICAL FORM
Sterile solution for intravenous infusion

CLINICAL PHARMACOLOGY

4.2. Posology and method of administration
Posology/frequency and duration of administration
The dosage is to be individualized by the physician depending on age, weight, clinical condition and in particular the patient’s hydration state. Serum electrolyte concentrations must be monitored during treatment.

In general, 500 to 3000 ml per 24 hours for adults, adolescents and elderly and 20 to 100 ml/kg per 24 hours for infants and children is recommended for treatment of isotonic extracellular dehydration and sodium depletion unless otherwise prescribed by the doctor.
The dosage when used as a diluent should be determined by the nature and the dose regimen of the diluted drug. In general 50 to 250 ml of fluid is sufficient.

The frequency of administration and dosage is adjusted by the physician according to the clinical condition of the patient.
When TURKFLEKS 0.9% ISOTONIC SODIUM CHLORIDE is used as a diluent, the infusion rate will be adjusted according to the nature and the dose regimen of the diluted drug.

Method of administration:
The administration is to be made by intravenous route in a peripheral or central vein using sterile, apyrogenic sets.
See also section 6.6 for details on the administration.

Additional information on special populations:
Renal/Hepatic failure:
No dosage recommendations are made for this patient group, as there is no specific study for this population.

Pediatric population:
As in adults, dosage and infusion rate are directed by a physician depending on weight, clinical and biological condition of the patient and the concomitant treatment.
In general 20 to 100 ml/kg per 24 h is recommended in this population.

Geriatric population:
As in adults, dosage and infusion rate are directed by a physician depending on weight, clinical and biological condition of the patient and the concomitant treatment.

Therapeutic indications
TURKFLEKS 0.9% ISOTONIC SODIUM CHLORIDE is indicated for:
- Treatment of isotonic extracellular dehydration
- Treatment of sodium depletion
- As diluent of compatible drugs for parenteral administration.

CONTRAINDICATIONS

The solution is contraindicated in patient presenting hypernatremia or hyperchloremia.
It is also contraindicated where the administration of sodium or chloride could be clinically detrimental.

Special warnings and precautions for use
The administration of intravenous solutions can cause fluid and/or solute overload resulting in dilution of serum electrolyte concentrations, overhydration, congested states or pulmonary edema. The risk of dilution is inversely proportional to the electrolyte concentration. The risk of congested states with peripheral and pulmonary edema is directly proportional to the electrolyte concentration.
The solution contains 154 mmol/l sodium (Na+) and 154 mmol/l chloride (Cl-); the osmolarity is about 308 mOsm/l and the pH is 5.5 (4.5-7.0).
Careful clinical monitoring is required at the beginning of any intravenous infusion.
Administrations should be periodically and carefully monitored. Clinical and biological parameters, in particular serum electrolyte concentrations should be monitored.
In preterm or term neonates, sodium retention can be seen because renal function is not yet fully developed. Repeated infusions of sodium chloride in neonates should therefore only be given after determination of the serum sodium levels.
Sodium-containing solutions should be used with caution in cases of hypertension, heart failure, peripheral or pulmonary edema, impaired renal function, preeclampsia, aldosteronism or other conditions and treatments with sodium accumulation (e.g. corticosteroid therapy).
Pseudohyponatremia is a condition in which plasma sodium is falsely low as measured by conventional methods in spite of the fact that it is not actually low. This may occur when large molecules are at a high concentration at an abnormally high level and, consequently, when the plasma water ratio falls abnormally. It has been reported that associated hyperlipemia and hyperproteinemia can also be seen in patients with diabetes mellitus. Real values can be obtained by evaluating the concentration based on plasma/water ratio.

Excessive administration of potassium-free solutions may result in significant hypokalemia. Serum potassium levels should be maintained and potassium supplemented as required.
To minimize the risk of possible incompatibilities arising from mixing any of these solutions with other additives that may be prescribed, the final mixture should be inspected for cloudiness or precipitation immediately after mixing, prior to administration and periodically during administration.
If administration is controlled by a pumping device, care must be taken to discontinue pumping action before the container runs dry or air embolism may result.

This solution is intended for intravenous administration using sterile equipment. It is recommended that intravenous administration apparatus be replaced at least once every 24 hours.
Use only if solution is clear and container and seals are intact.
Laboratory tests:
Clinical evaluation and periodic laboratory determinations are necessary to monitor changes in fluid balance, electrolyte concentrations, and acid-base balance during prolonged parenteral therapy or whenever the condition of the patient warrants such evaluation. Significant deviations from normal concentrations may require normalization of these values with alternative solutions.
Warnings and precautions for pediatric use:
In neonates or in very small infants even small volumes of fluid may affect fluid and electrolyte balance. Care must be exercised in treatment of neonates, especially pre-term neonates, whose renal function may be immature and whose ability to excrete fluid and solute loads may be limited. Fluid intake, urine output, and serum electrolytes should be monitored closely.
Warnings and precautions for use in elderly:
In general, dose selection for an elderly patient should be cautious. Starting at the low end of the dosing range is recommended in elderly considering the greater frequency of decreased hepatic, renal, or cardiac function, and of concomitant disease or other drug therapy.

OTHER SAFETY INFORMATION

Interaction with other medicinal products and other forms of interaction
Some of the drugs and solutions added to the solution may be incompatible. As in all parenteral solutions, compatibility with additional medication should be evaluated by the physician.
If other substances are to be added to the solution, aseptic technique should be used and shaken until mixed. It should be ensured that there is no discoloration, insoluble particles and crystallization after the drugs are added into TURKFLEKS 0.9% ISOTONIC SODIUM CHLORIDE.
Caution should be exercised because of the risk of sodium and water retention when used with corticosteroids and carbenoxolone due to its sodium content.

Special populations:
No interaction studies have been performed with TURKFLEKS 0.9% ISOTONIC SODIUM CHLORIDE on special population.
Pediatric population:
No interaction studies have been performed with TURKFLEKS 0.9% ISOTONIC SODIUM CHLORIDE in the pediatric population.

PREGNANCY

General recommendation
Pregnancy category: C
Women with childbearing potential/Contraception
No effects of TURKFLEKS 0.9% ISOTONIC SODIUM CHLORIDE on women of childbearing potential or interaction with drugs used for birth control (contraception) have been reported.
Pregnancy
There are no adequate data from the use of isotonic sodium chloride solutions in pregnant women.
Studies on animals are insufficient in terms of effects on pregnancy / and - or / embryonal / fetal development / and - or / birth / and - or postnatal development. (See section 5.3). Potential risk for human is unknown.
TURKFLEKS 0.9% ISOTONIC SODIUM CHLORIDE should not be used during pregnancy unless it is necessary for life-threatening conditions.
Animal reproduction studies have not been conducted with sodium chloride containing solutions.
It is also not known whether TURKFLEKS 0.9% ISOTONIC SODIUM CHLORIDE can cause fetal harm when administered to a pregnant woman or can affect reproduction capacity.
TURKFLEKS 0.9% ISOTONIC SODIUM CHLORIDE should be given to a pregnant woman only if clearly needed.
Delivery:
The effects of TURKFLEKS 0.9% ISOTONIC SODIUM CHLORIDE on the duration of labor or delivery, on the possibility that forceps delivery or other intervention or resuscitation of thenewborn will be necessary, and on the later growth, development, and functional maturation of the child are unknown.
Administration of sodium and dextrose containing solutions during labor and delivery have been reported in the literature. Caution should be exercised, and the fluid balance, glucose and electrolyte concentrations, and acid-base balance, of both mother and fetus should be evaluated periodically or whenever warranted by the condition of the patient or fetus.

LACTATION

It is not known whether this drug is excreted in human milk. Because many drugs are excreted in human milk, caution should be exercised when TURKFLEKS 0.9% ISOTONIC SODIUM CHLORIDE is administered to a nursing woman.

FEMALES AND MALES OF REPRODUCTIVE POTENTIAL

There are no data on the effects of sodium chloride solutions on fertility.

ADVERSE REACTIONS

Undesirable effects are not expected in normal conditions of treatment.
Undesirable effects may result from an excess or deficit of one or more of the ions present in the solution; therefore, frequent monitoring of electrolyte levels is essential. The physician should also be alert to the possibility of adverse reactions to drug additives. Prescribing information for drug additives to be administered in this manner should be consulted. Injudicious intravenous sodium chloride therapy (e.g. post-operatively and in patients with impaired cardiac or renal function) may cause hypernatraemia. Osmotically induced water shifts decrease intracellular volume, resulting in dehydration of internal organs, especially the brain, which may lead to thrombosis and haemorrhage.
If administered sub-cutaneously, any addition to the isotonic solution could render it hypertonic and cause pain at the site of injection.
Administration of large doses may give rise to sodium accumulation, oedema, and hyperchloraemic acidosis.

If an adverse reaction does occur during administration, discontinue the infusion, evaluate the patient, institute appropriate therapeutic countermeasures.
The displayed frequency categories use the following convention: Very common (≥ 1/10); common (≥ 1/100 to < 1/10); uncommon (≥ 1/1,000 to < 1/100); rare (≥ 1/10,000 to <1/1,000); very rare (<1/10,000), not known (cannot be estimated form the available data). The following adverse reactions are those that may result in an excess of sodium or chloride due to overdose, or may be due to administration technique. The frequency of these side effects is not known (it can be seen in as few patients as cannot be identified with the available data).
Blood and lymphatic system disorders
Not known: Thrombosis; hemorrhage
Metabolism and nutrition disorders
Not known: Sodium accumulation; Water retention and edema; Exacerbation of congestive heart failure (due to hypernatremia); Hyperchloremic acidosis.
Nervous system disorders
Not known: Headache, dizziness, restlessness, irritation, convulsions, coma and death (dehydration of the brain associated with hypernatremia).

Cardiac disorders
Not known: Tachycardia (associated with hypernatremia).
Vascular disorders
Not known: Hypertension (associated with hypernatremia).
Respiratory, thoracic and mediastinal disorders
Not known: Pulmonary edema, respiratory depression and respiratory arrest (associated with hypernatremia).
Gastrointestinal disorders
Not known: Nausea, vomiting, diarrhea, abdominal cramps, feeling of thirst, decreased salivation (associated with hypernatremia).
Skin and subcutaneous tissue disorders
Not known: Decreased perspiration (associated with hypernatremia).

Musculoskeletal and connective tissue disorders
Not known: Muscle twitching and rigidity (associated with hypernatremia).
Renal and urinary disorders
Not known: Renal failure (associated with hypernatremia)
General disorders and administration site conditions
Not known: Fever; Fatigue (due to hypernatremia); Pain at the injection site (due to subcutaneous administration of hypertonic solution with additions).
Surgical and medical procedures
Not known: Febrile reactions; infection at the site of injection, venous thrombosis or phlebitis extending from the site of injection; extravasation and hypervolemia (adverse effects that can be seen due to the technique of administration).

OVERDOSAGE

Adverse reactions of sodium excess in the body include nausea, vomiting, diarrhea, abdominal cramps, thirst, reduced salivation, lacrimation and sweating, fever, tachycardia, hypertension, renal failure, peripheral and pulmonary oedema, respiratory arrest, headache, dizziness, restlessness, irritability, fatigue, muscular twitching and rigidity, convulsions, coma, and death.
Excess chloride accumulation in the body may cause a loss of bicarbonate with an acidifying effect on body fluids.
In the event of a fluid or solute overload during parenteral therapy, reevaluate the patient's condition and institute appropriate corrective treatment.
Diuretics may be used in the treatment of oedema associated with isotonic expansion and appropriate replacement therapy which will not cause fluid electrolyte imbalance should be applied.
Treatment of hypervolemic hypernatremia requires removal of more sodium than water from the body and diuretic-induced sodium and water loss can only be met by water. The main purpose of the treatment is to normalize the volume and composition of body fluids.
When overdose is related to medicinal products added to the solution infused, the signs and symptoms of over infusion will be related to the nature of the additive being used. In the event of accidental over infusion, treatment should be discontinued and the patient should be observed for the appropriate signs and symptoms related to the drug administered. The relevant symptomatic and supportive measures should be provided as necessary.

PHARMACODYNAMICS

Pharmacotherapeutic group: Intravenous solutions/Solutions affecting electrolyte balance
ATC code: B05XA03
TURKFLEKS 0.9% ISOTONIC SODIUM CHLORIDE is an isotonic solution, with an approximate osmolarity of 308 mOsm/l.
The pharmacodynamic properties of the solution are those of the sodium and chloride ions in maintaining the fluid and electrolyte balance.
Ions, such as sodium, circulate through the cell membrane, using various mechanisms of transport, among which is the sodium pump (Na-K-ATPase) Sodium plays an important role in neurotransmission, cardiac electrophysiology and in renal metabolism.
Chloride is mainly an extracellular anion. Intracellular chloride is in high concentration in red blood cells and gastric mucosa. Reabsorption of chloride follows reabsorption of sodium.
The pharmacodynamic properties of the added drugs are the same as the pharmacodynamic properties of the added drug.

PHARMACOKINETICS

General properties
Pharmacokinetic properties of TURKFLEKS 0.9% ISOTONIC SODIUM CHLORIDE are those of its components (sodium and chloride).
Absorption:
Active substances in drugs administered intravenously reach their maximum plasma concentrations immediately after administration.
Distribution:
Sodium distribution varies according to tissues: it is fast in muscles, liver, kidney, cartilage and skin; it is slow in erythrocytes and neurons; it is very slow in the bone.
Chloride is mainly distributed in extracellular fluids.
Biotransformation:
The half-life after radioactively labeled sodium (24Na) injection is 11-13 days for 99% of injected sodium and one year for the remaining 1%.

Chloride closely monitors sodium metabolism and changes in the acid-base balance of the body are reflected by changes in chloride concentration.
Elimination:
Sodium is excreted primarily by the renal route, but at the same time the vast majority is reabsorbed by the renal route. A small amount of sodium is excreted with feces and sweat.
Since chloride metabolically monitors sodium, it is mainly excreted by the renal route but also in lesser amounts in feces and sweat.
Linearity/Non-linearity:
Electrolytes in the TURKFLEKS 0.9% ISOTONIC SODIUM CHLORIDE composition show a linear pharmacokinetic behavior when administered to the body at therapeutic doses to complete their deficiency.

CLINICAL STUDIES

Because the components of the solution are physiological components of human and animal plasma and are not expected to show toxic effects in clinical practice, studies with TURKFLEKS 0.9% ISOTONIC SODIUM CHLORIDE have not been performed to evaluate the effects of carcinogenic, mutagenic potential and fertility.
The safety of medications added into the solution must be considered separately.

OTHER SAFETY INFORMATION

Incompatibilities
Incompatibility of the medicinal product to be added with the solution must be assessed before addition. In the absence of compatibility data, this solution must not be mixed with other medicinal products.
It is the responsibility of the physician to judge the incompatibility of an additive medication with the solution by checking for eventual color change and/or eventual precipitate, insoluble complexes or crystals apparition. The prescribing information of the drug to be added to TURKFLEKS 0.9% ISOTONIC SODIUM CHLORIDE must be consulted to decide whether the additive is compatible.

Before adding a drug, its solubility and stability at the pH of TURKFLEKS 0.9% ISOTONIC SODIUM CHLORIDE should be verified.
TURKFLEKS 0.9% ISOTONIC SODIUM CHLORIDE should be immediately used following the addition of a compatible drug.
Those additives known to be incompatible should not be used.
6.3. Shelf life
36 months.
Shelf life during use for dilution:
From a microbiological point of view, the product should be used immediately. If not used immediately, in-use storage times and conditions prior to use are the responsibility of the user and would normally not be longer than 24 hours at 2 to 8°C, unless reconstitution has taken place in controlled and validated aseptic conditions.
6.4. Special precautions for storage
There are no special conditions for storage. It must be kept at room temperature under 30 °C.
6.5. Nature and contents of container
50, 100, 150, 250, 500, 1000 and 3000 ml PP (polypropylene) bags
Product has in two forms: with and without set.

DISPOSAL AND WASTE HANDLING

Directions for use
Solution should be inspected visually before use.
The administration is by intravenous route with sterile sets.
Only products that are clear, particle-free and intact in packaging integrity should be used.
The administration should be started as soon as possible after the application set is attached to the product.
In order to prevent an air embolisation that may occur due to the residual air in the bag, no serial connection should be made with other infusion fluids.

Pressurizing intravenous solutions contained in flexible plastic containers to increase flow rates can result in air embolism if the residual air in the container is not fully evacuated prior to administration.
The solution should be applied using the aseptic technique through the sterile application set. In order to prevent air from entering the system, liquid must be passed through the application set before use.
Additional medication may be added before and during infusion with the aid of injection a needle in aseptic conditions. The final product’s isotonicity should be determined before parenteral administration.
The added drug must be completely mixed with the solution before application to the patient. Solutions containing additives should be used immediately and not stored.
Adding other medication or using an incorrect administration technique might cause the appearance of fever reactions due to the possible introduction of pyrogens. In case of adverse reaction, infusion must be stopped immediately.
For single use.
Do not store partially used solutions.
Do not reconnect partially used bags.

INSTRUCTIONS FOR USE

To open:
1. Check the integrity of the outer packaging and check for leaks; do not use if the packaging is damaged.
2. Tear off the protective outer packaging.
3. Check for minute leaks by squeezing inner bag firmly. Check solution for limpidity and absence of foreign matter.

Preparation for administration:
1. Suspend the bag.
2. Remove the protector from application port.
3. Stick the spike of the application set firmly in the application tip.
4. The instructions for use of the set must be followed for the administration of the solution.

Addition of additional drug:
Attention: As with all parenteral solutions, all substances to be added to the product must be compatible with the product. If an addition is to be made, compatibility should be checked in the final mixture before administration to the patient.

Adding medication before administration
1. Disinfect medication site.
2. Using syringe with 19 to 22 gauge needle, puncture resealable medication port and inject.
3. Mix the solution and the added drug thoroughly. For high density medication such as potassium chloride, tap gently to the ports of the bag, while ports are upright to allow mixing.

Attention: Do not store bags containing added medications.
Adding medication during administration
1. Close the clamp.
2. Disinfect medication site.
3. Inject the drug to be added using syringe with 19 to 22 gauge needle.
4. Remove container from IV pole and/or turn to an upright position.
5. In this position, tap gently both ports to allow mixing of solution and medication.
6. Return bag to its former position and open the clamp and continue administration.

HEALTH CARE PROVIDER LETTER

April 02, 2025

Subject: Temporary importation of 0.9% Isotonic Sodium Chloride Injection from Turk Ilac located in Ankara-TURKEY to address drug shortages per https://dps.fda.gov/drugshortages/activeingredient/sodium-chloride-09--injection

To prevent a shortage of large volume parenteral fluid drug products, Turk Ilac ve Serum Sanayi is coordinating with the U.S. Food and Drug Administration (FDA) to temporarily import 0.9% Isotonic Sodium Chloride Injection (50ml, 100ml, 150ml, 250ml, 500ml, 1000 ml, and 3000ml) from Turk Ilac ve Serum Sanayi manufacturing facility located in Ankara/TURKEY. FDA has not approved these products manufactured by Turk Ilac ve Serum Sanayi.

Effective immediately, and during this temporary period, Turk Ilac ve Serum Sanayi will offer the following imported product from Turk Ilac ve Serum Sanayi facility located in Ankara/TURKEY:

Product Name and Description | Volume | Bags per Box | NDC Code
Turkfleks %0.9 Isotonic Sodium Chloride | 50ml | 100 | 85160-400-10
Turkfleks %0.9 Isotonic Sodium Chloride | 100ml | 50 | 85160-400-20
Turkfleks %0.9 Isotonic Sodium Chloride | 150ml | 50 | 85160-400-30
Turkfleks %0.9 Isotonic Sodium Chloride | 250ml | 25 | 85160-400-40
Turkfleks %0.9 Isotonic Sodium Chloride | 500ml | 20 | 85160-400-50
Turkfleks %0.9 Isotonic Sodium Chloride | 1000ml | 20 | 85160-400-60
Turkfleks %0.9 Isotonic Sodium Chloride | 3000ml | 10 | 85160-400-70

Please note the following:

- Upon receiving Submission Acceptance Turk Ilac ve Serum Sanayi will have bag labels written in both Turkish and English.
- The bag labels will contain the active pharmaceutical ingredient, concentration, volume, and NDC code in English.
- The imported products' administration port system is fully compatible with sets marketed in the United States.
- The imported products use a carton box that is taped closed. To avoid damage to the solution container, take care not to use sharp instruments to open the box.
- The imported products do not contain barcodes on the unit label. Alternative procedures should be followed to ensure that the correct drug product is being used in all systems and processes and administered to individual patients. For example, institutions should consider manually inputting the product into their systems and confirm that barcode systems do not provide incorrect information when the product is scanned.
- 0.9% Isotonic Sodium Chloride Injection is available only by prescription in the United States. However, the imported products do not have the statement "Rx only" on the labeling.
- USE A NEW BAG IF PARTICULATES ARE VISIBLE OR IF THE IV BAG CONTAINS A LEAK.

Additional key differences in the labeling between the FDA-approved product and the imported products are stated in the product comparison table at the end of this letter as follows:

Table 1. Key differences between FDA-approved and Turkfleks 0.9% Isotonic Sodium Chloride Injection

Table 2. Label images of FDA-approved and Turkfleks 0.9% Isotonic Sodium Chloride Injection

Reporting Adverse Events or Product Quality Issues

To report adverse events associated with these imported products, please use the contact us at info@turkilac.com.tr.

Adverse events or quality problems experienced with the use of these imported products may also be reported to the FDA's MedWatch Adverse Event Reporting program either online, by regular mail or by fax:

- Complete and submit the report Online: www.fda.gov/medwatch/report.htm
- Regular mail or Fax: Download form www.fda.gov/MedWatch/getforms.htm

or call 1-800332-1088 to request a reporting form, then complete and return to the address on the preaddressed form or submit by fax to 1-800-FDA-0178 (1-800-332-0178).

Sincerely,

Mehmet Berat Battal

Table 1: Key Differences between FDA Approved product and Turkfleks %0.9 Isotonic Sodium Chloride

 | FDA- Approved Product | Turkfleks Import from Turkey
Product Name | 0.9% Sodium Chloride injection USP* | %0.9 Isotonic Sodium Chloride Injection
Label Volume | 50 mL, 100 mL, 150 mL, 250 mL, 500 mL, 1000 mL | 50 mL, 100 mL, 150 mL, 250 mL, 500 mL, 1000 mL, 3000 mL
Language of the Labels | English | Turkish
Indications | Sodium Chloride Injection, USP is indicated as a source of water and electrolytes. 0.9% Sodium Chloride. Injection, USP is also indicated for use as a priming solution in hemodialysis procedures. | Source of water for electrolytes and:; - In the treatment of isotonic extracellular dehydration; - In the treatment of sodium losses; - As a diluent solution for drugs with which it is compatible in parenteral applications
Active Ingredients | Each 100 ml contains 0.9g Sodium Chloride, USP | Each 100 ml contains 9g Sodium Chloride
Additional Information | pH is 5.6 (4.5-7.0) Osmolarity 310 mOsm/L (calc) | pH is 5.5 (4.5-7.0) Osmolarity 308 mOsm/L (calc)
Store Conditions | Store at room temperature 25C/77F | Store at below 30C
Container Type | ethylene and propylene | Polypropylene

*Description states: Sodium Chloride Injections USP are sterile, nonpyrogenic, isotonic and contain no bacteriostatic or antimicrobial agents.

Table 2: Label Images of FDA-approved and Turkfleks %0.9 Isotonic Sodium Chloride Injection

FDA-approved Product | Turkfleks %0.9 Isotonic Sodium Chloride Injection